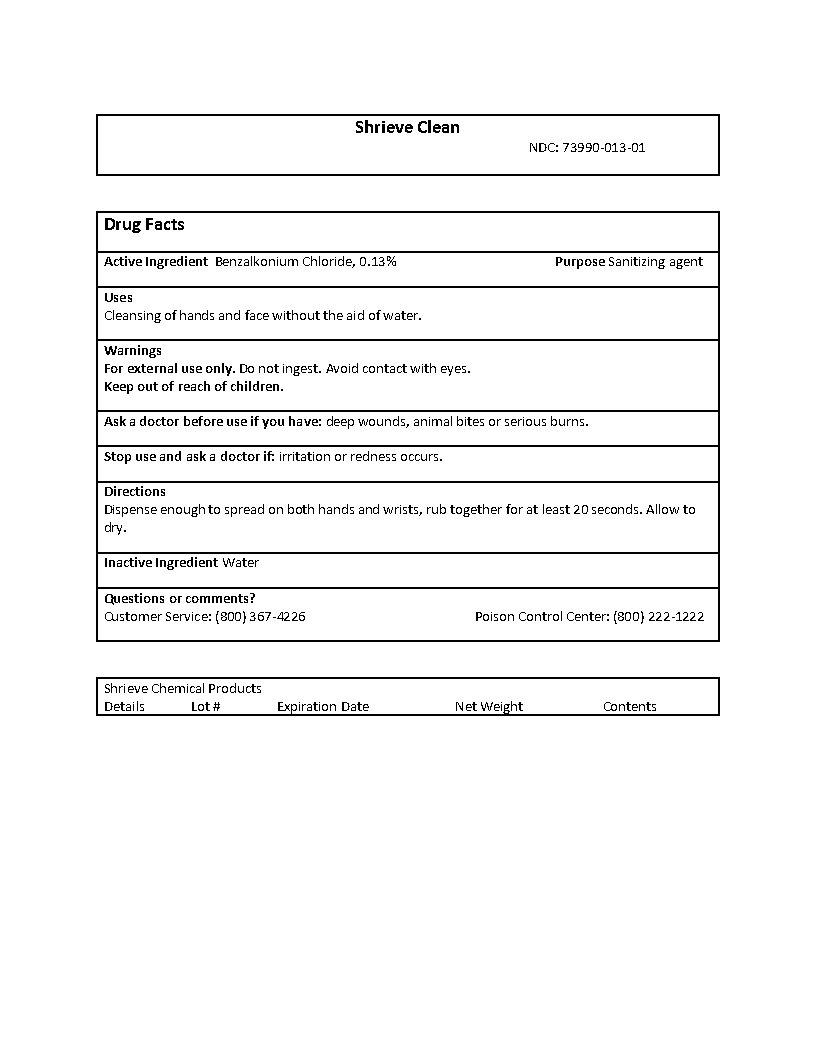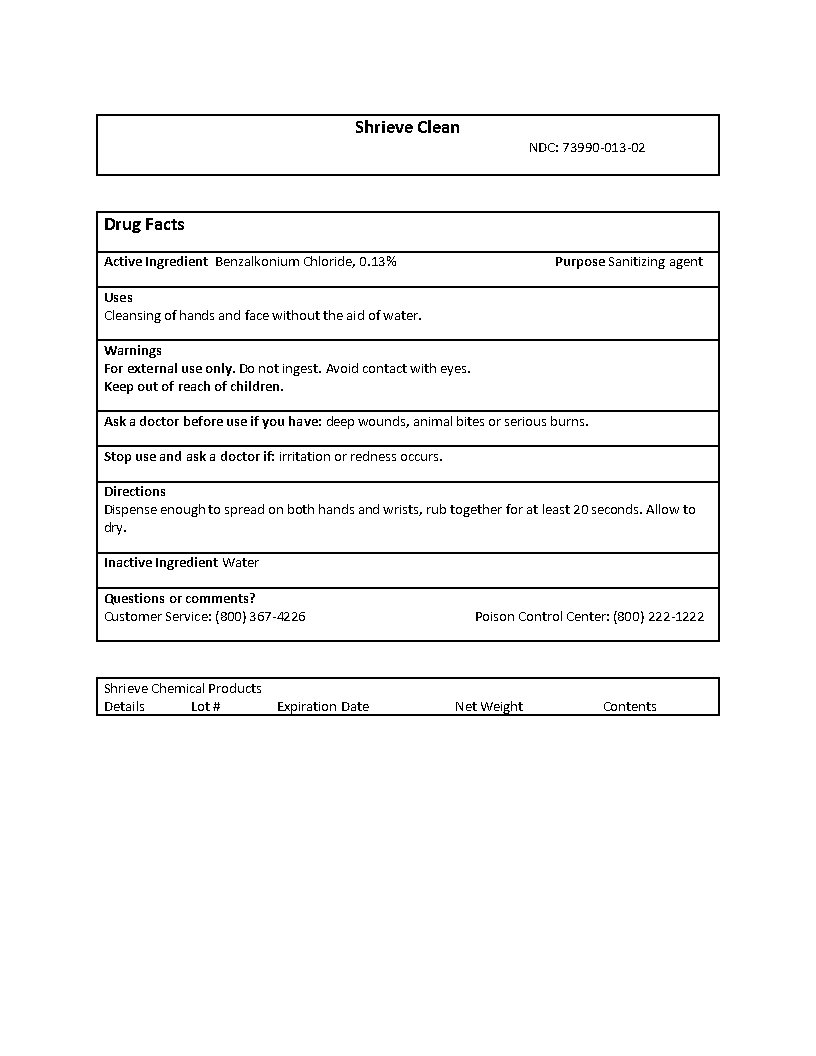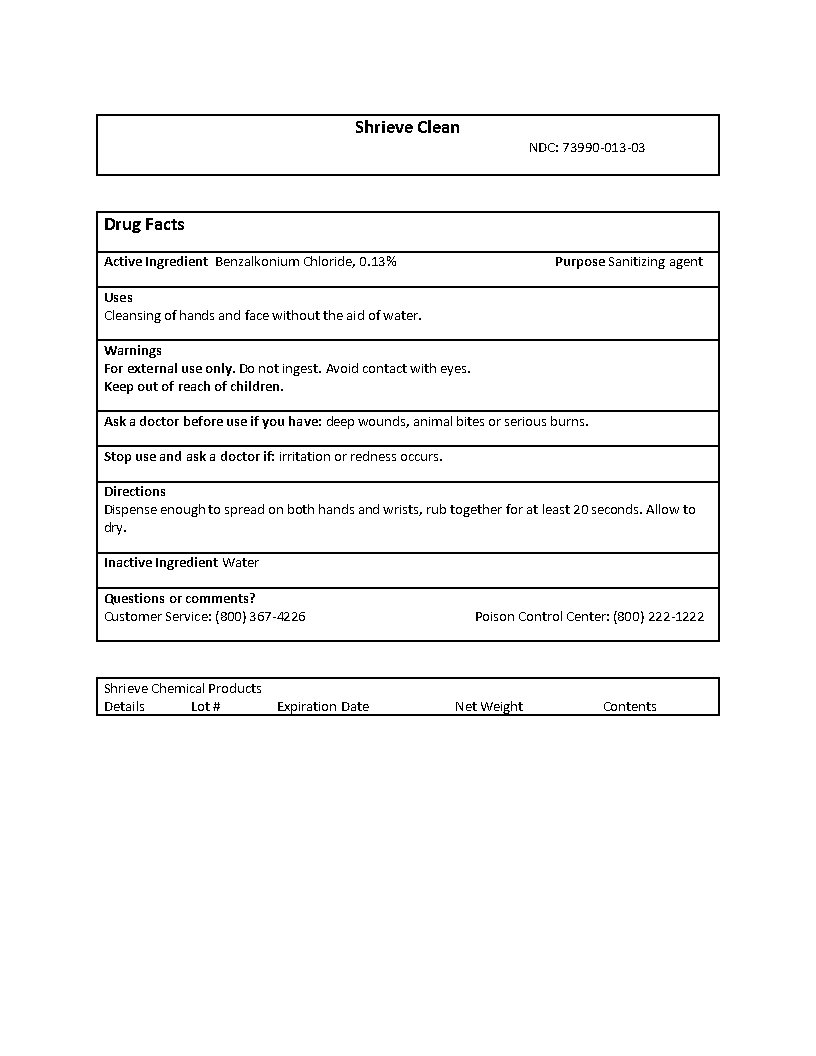 DRUG LABEL: Shrieve Clean
NDC: 73990-013 | Form: LIQUID
Manufacturer: Shrieve Chemical Services - Us, LLC
Category: otc | Type: HUMAN OTC DRUG LABEL
Date: 20200330

ACTIVE INGREDIENTS: BENZALKONIUM CHLORIDE 0.13 1/1 1
INACTIVE INGREDIENTS: WATER

Hand sanitizer

73990-013 Shrieve Clean

Benzelkonium Chloride @ 0.13%. Purpose: Sanitizing agent.

Shrieve Clean

73990-013-03 - 208.175L (55 gal).
73990-013-03 - Shrieve Clean label.jpg

73990-013-02 - 18.925L (5 gal).
73990-013-02 - Shrieve Clean label.jpg

73990-013-01 - 3.785L (1 gal).

73990-013-01 - Shrieve Clean label.jpg

DOSAGE & ADMINISTRATION SECTION

Dispense enough to spread on both hands and wrists, rub together for at least 20 seconds. Allow to dry.

WARNINGS SECTION

Warnings
For external use only.
Do not ingest.
Avoid contact with eyes.

INACTIVE INGREDIENT SECTION

Inactive Ingredient
Water @ 99.87%

INDICATIONS & USAGE SECTION

Uses
Cleansing of hands and face without the aid of water.

OTC - KEEP OUT OF REACH OF CHILDREN

Keep out of reach of children.

OTC - PURPOSE SECTION

Purpose
Sanitizing agent

PACKAGE LABEL.PRINCIPAL DISPLAY PANEL

Drug Facts
Active IngredientBenzalkoniumChloride, 0.13%

Purpose Sanitizing agent
Uses Cleansing of hands and face without the aid of water.
Warnings For external use only.Do not ingest. Avoid contact with eyes. Keep out of reach of children. Ask a doctor before use if you have: deep wounds, animal bites or serious burns.Stop use and ask a doctor if: irritation or redness occurs.
Directions Dispense enough to spread on both hands and wrists, rub together for at least 20 seconds. Allow to dry.
Inactive Ingredient Water
Questions or comments? Customer Service: (800) 367-4226 Poison Control Center: (800) 222-1222
Shrieve Chemical Products
DetailsLot # Expiration Date Net Weight Contents